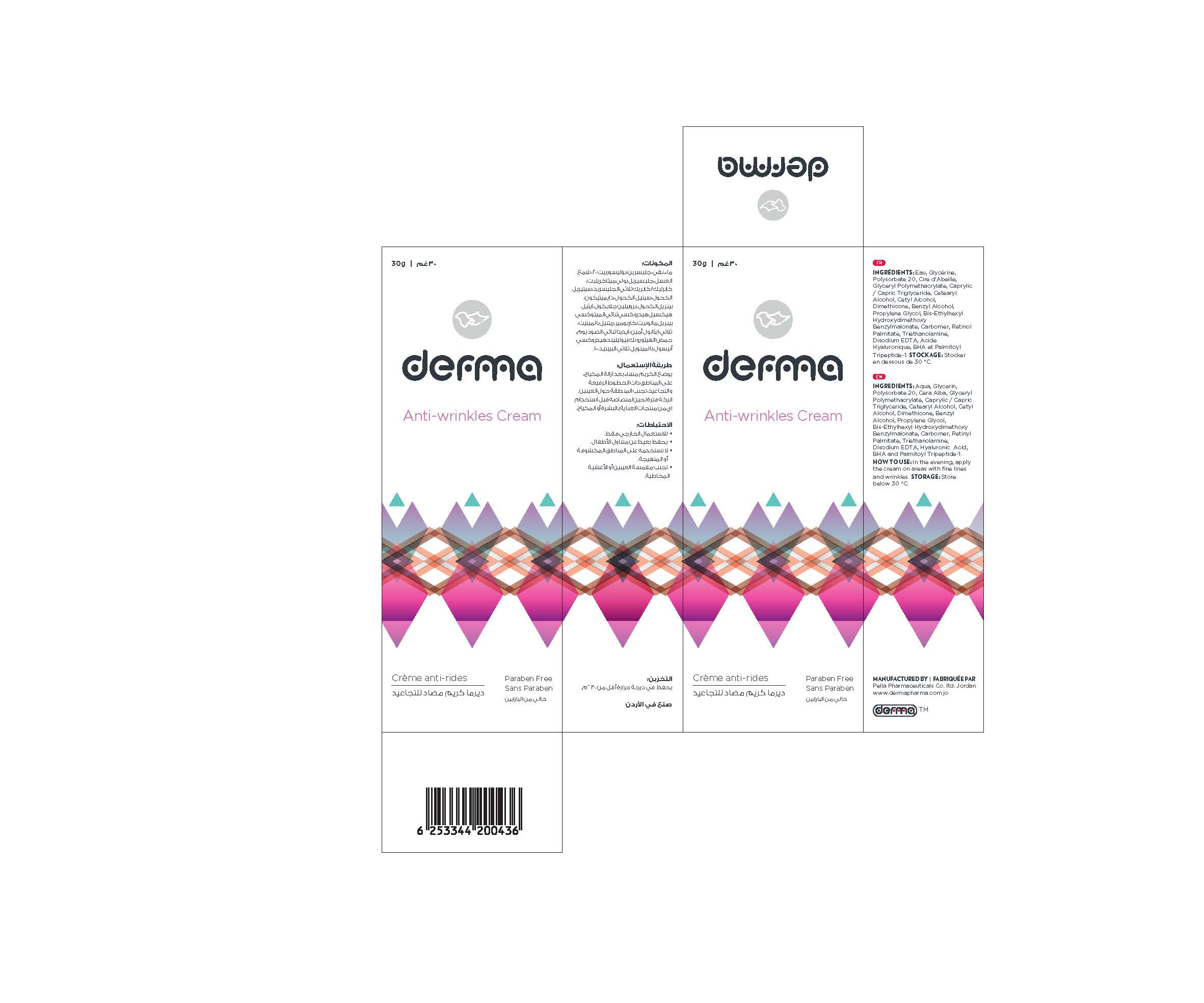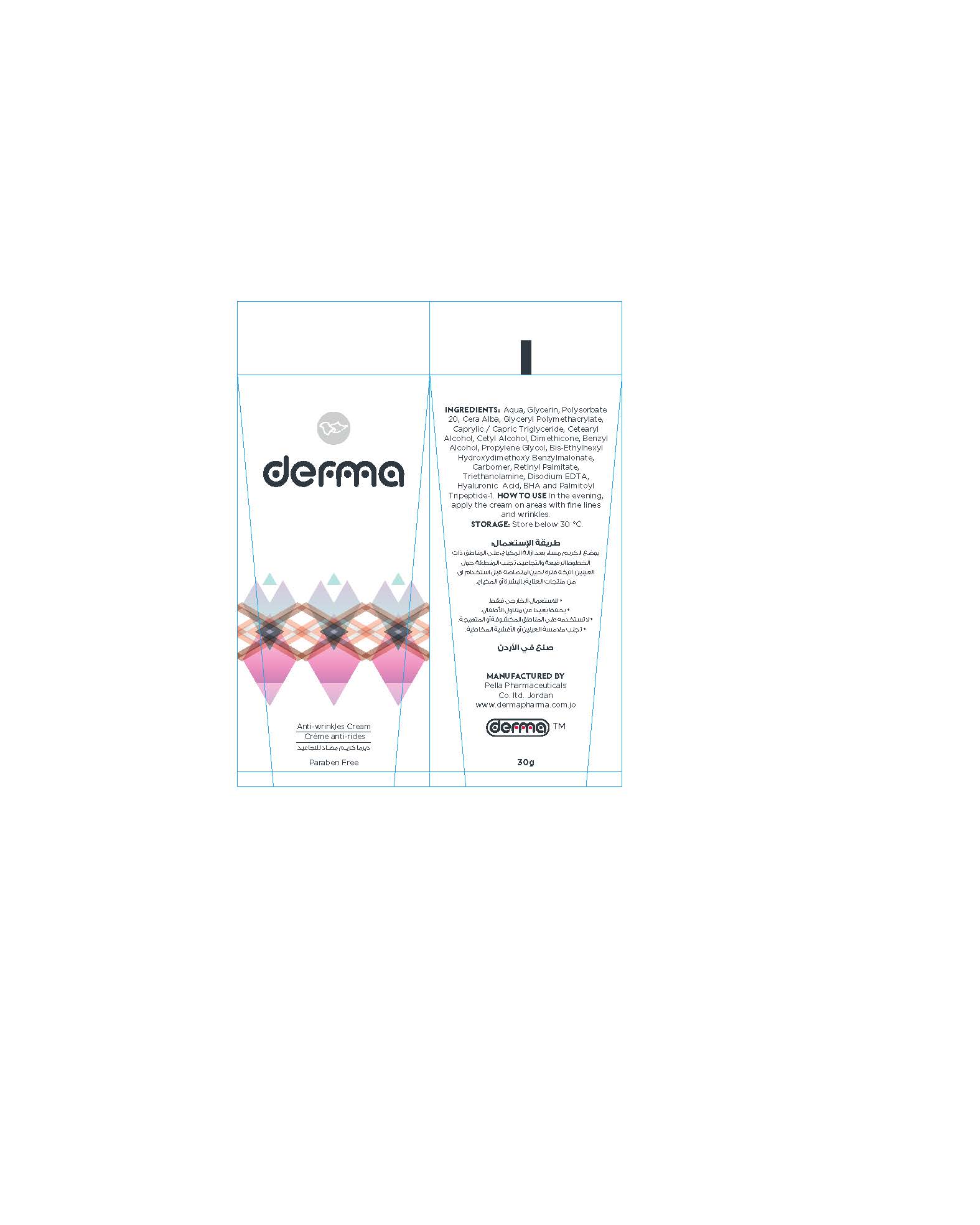 DRUG LABEL: Derma Anti-Wrinkles
NDC: 82160-436 | Form: CREAM
Manufacturer: Pella Pharmaceuticals Co. Ltd
Category: otc | Type: HUMAN OTC DRUG LABEL
Date: 20211129

ACTIVE INGREDIENTS: PALMITOYL TRIPEPTIDE-1 0.0009 mg/30 g; HYALURONIC ACID 0.3 mg/30 g; VITAMIN A PALMITATE 0.9 mg/30 g
INACTIVE INGREDIENTS: MEDIUM-CHAIN TRIGLYCERIDES; WHITE WAX; BUTYLATED HYDROXYANISOLE; EDETATE DISODIUM ANHYDROUS; DIMETHICONE 100; WATER; BENZYL ALCOHOL; PROPYLENE GLYCOL; GLYCERIN; POLYSORBATE 20; CETOSTEARYL ALCOHOL; CETYL ALCOHOL; CARBOMER 940; BIS-ETHYLHEXYL HYDROXYDIMETHOXY BENZYLMALONATE; TROLAMINE

Anti-Wrinkles

Forms and presentation

Cream: Tube of 30 g.

Active Ingredients

Bis-Ethylhexyl Hydroxydimethoxy Benzylmalonate

Retinyl Palmitate (Vitamin A)

Hyaluronic Acid

Palmitoyl Tripeptide-1

Inactive ingredients

Aqua, Glycerin, Polysorbate 20, Cera Alba, Glyceryl Polymethacrylate, Caprylic / Capric Triglyceride, Cetearyl Alcohol, Cetyl Alcohol, Dimethicone, Benzyl Alcohol, Propylene Glycol, Carbomer, Triethanolamine, Disodium EDTA and BHA .

Purpose

Anti-Wrinkles

Properties

It is a cream with a powerful formula that refill wrinkles from the inside.
Paraben free.

Indications

Anti-wrinkles Cream

Precaution

Keep out of reach of children

Warnings

- For external use only
- Avoid contact with eyes and mucous membranes.

Contraindications

Hypersensitivity to any of the components.

Side effects

There are no known side effects.

Dosage and administration

In the evening, apply the cream on areas with fine lines and wrinkles. Avoid the area around the eyes. Leave it until absorbed before using any of the make-up or skin care products.

Storage conditions

Store at a temperature below 30 °C.